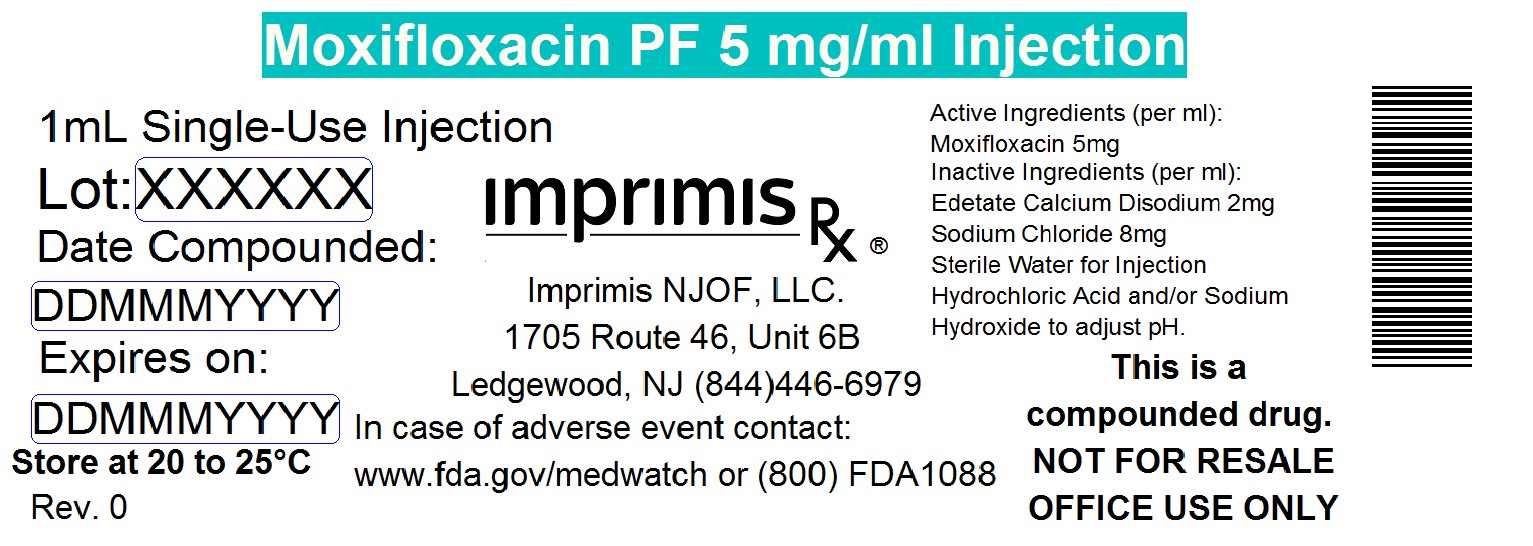 DRUG LABEL: Moxifloxacin PF
NDC: 71384-511 | Form: INJECTION, SOLUTION
Manufacturer: Imprimis NJOF, LLC
Category: prescription | Type: HUMAN PRESCRIPTION DRUG LABEL
Date: 20200303

ACTIVE INGREDIENTS: MOXIFLOXACIN HYDROCHLORIDE MONOHYDRATE 5 mg/1 mL

STORAGE AND HANDLING

20^0 to 25^0 C (*68^0 to 77^0 F)